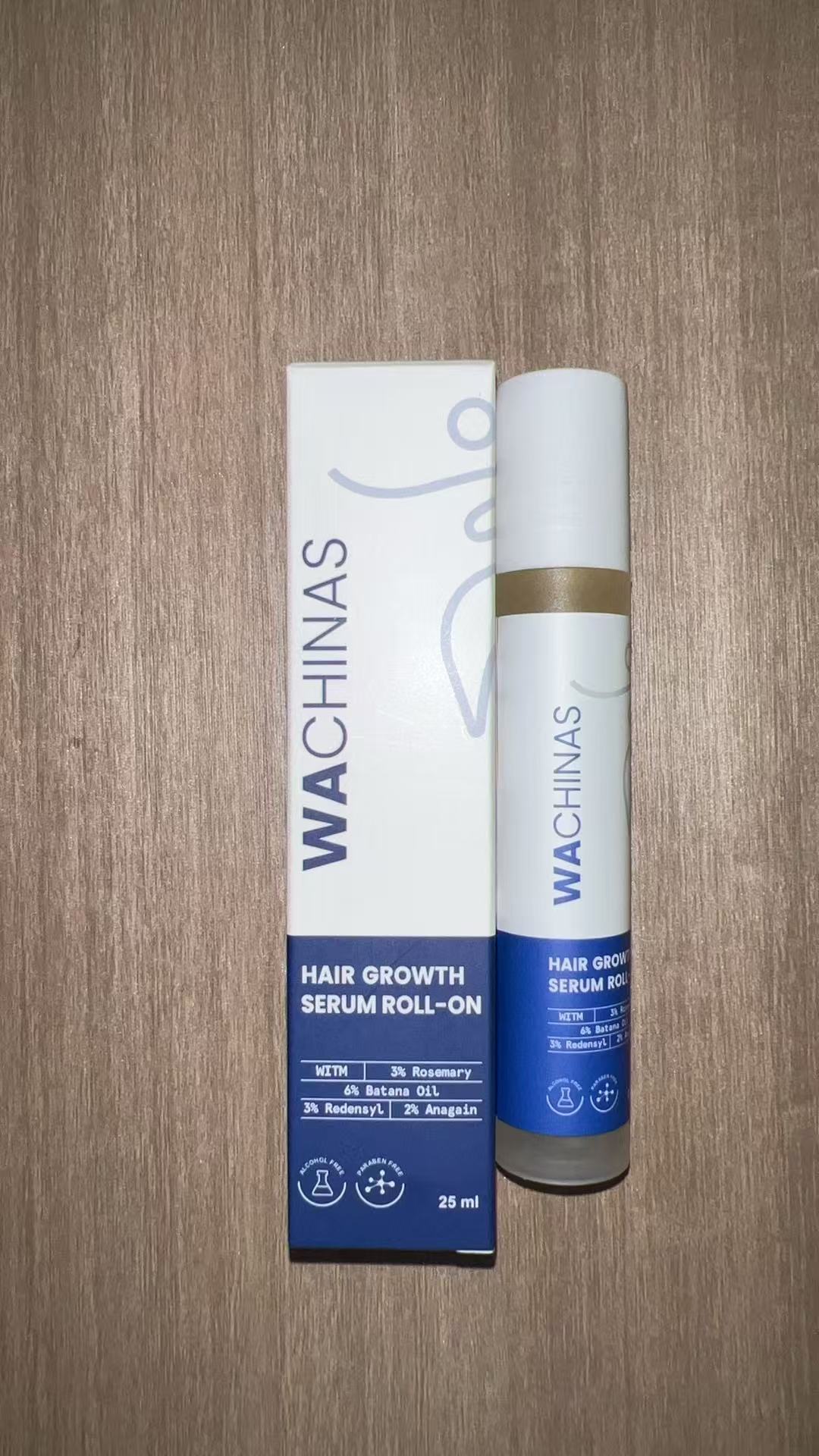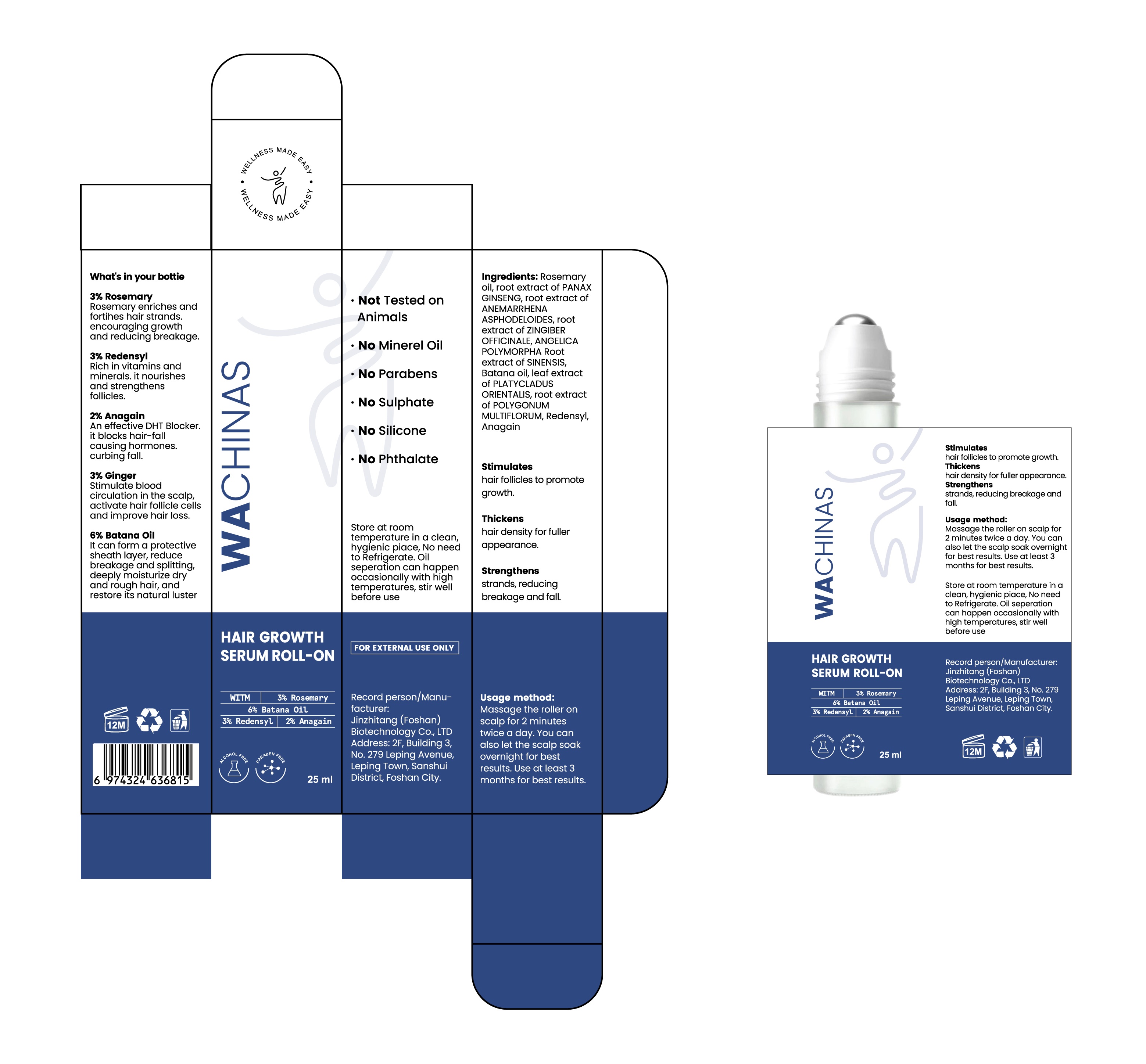 DRUG LABEL: HAIR GROWTH SERUM ROLL-ON
NDC: 87104-0201 | Form: LIQUID
Manufacturer: Jinzhitang (Foshan) Biotechnology Co., Ltd.
Category: otc | Type: HUMAN OTC DRUG LABEL
Date: 20251029

ACTIVE INGREDIENTS: ROSEMARY OIL 750 mg/25 mL
INACTIVE INGREDIENTS: GINGER 750 mg/25 mL

HAIR GROWTH SERUM ROLL-ON

WARNINGS AND PRECAUTIONS

1. FOR EXTERNAL USE ONLY

DOSAGE AND ADMINISTRATION

1. 3% Rosemary oil
2. 3% Redensyl
3. 2% Anagai
4. 3% Ginger

WARNINGS

1. FOR EXTERNAL USE ONLY

INACTIVE INGREDIENT

1. root extract of PANAX GINSENG
2. root extract of ANEMARRHENA ASPHODELOIDES
3. root extract of ZINGIBER OFFICINALE
4. ANGELICA POLYMORPHA Root extract of SINENSIS
5. leaf extract of PLATYCLADUS ORIENTALIS
6. root extract of POLYGONUM MULTIFLORUM

KEEP OUT OF REACH OF CHILDREN

PURPOSE

Stimulates:

hair folicles to promote growth.
Thickens:

hair density for fullerappearance.
Strengthens:

strands reducing breakage and fall

INDICATIONS AND USAGE

- Usage method:Massage the roller onscalp for 2 minutestwice a day. You canalso let the scalp soakovernight for bestresults. Use at least 3months for best results.

psakage label

1. 3% Rosemary:Rosemary enriches andfortihes hair strands.encouraging growthand reducing breakage.
2. 3% RedensylRich in vitamins andminerals.it nourishesand strengthensfollicles.
3. 2% Anagain:An effective DHT Blockerit blocks hair-fallcausing hormones.curbing fall.
4. 3% Ginger:Stimulate bloodcirculation in the scalp.activate hair follicle cellsand improve hair loss.
5. 6% Batana Oil:It can form a protectivesheath layer, reducebreakage and splitting,deeply moisturize dryand rough hair, andrestore its natural luster